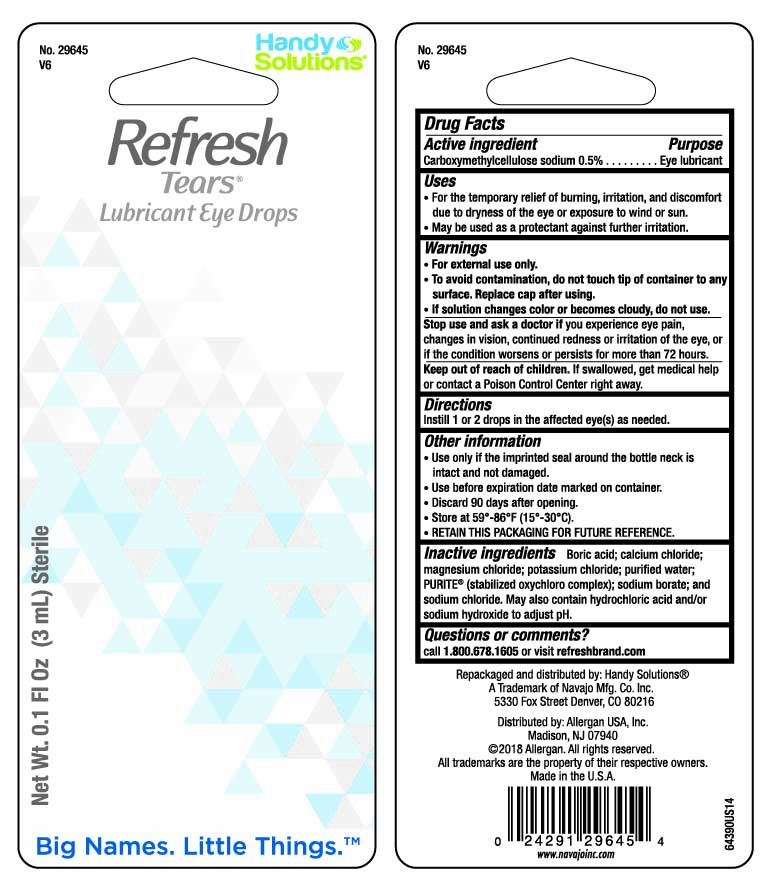 DRUG LABEL: Refresh Tears Lubricant
NDC: 67751-130 | Form: SOLUTION/ DROPS
Manufacturer: Navajo Manufacturing Company Inc.
Category: otc | Type: HUMAN OTC DRUG LABEL
Date: 20241002

ACTIVE INGREDIENTS: CARBOXYMETHYLCELLULOSE SODIUM 5 mg/1 mL
INACTIVE INGREDIENTS: BORIC ACID; CALCIUM CHLORIDE; MAGNESIUM CHLORIDE; POTASSIUM CHLORIDE; WATER; SODIUM CHLORITE; SODIUM BORATE; SODIUM CHLORIDE; HYDROCHLORIC ACID; SODIUM HYDROXIDE

Refresh Tears Lubricant Eye Drops

Active ingredient

Carboxymethylcellulose sodium 0.5%

Purpose

Eye lubricant

Uses

- For the temporary relief of burning, irritation, and discomfort due to dryness of the eye or exposure to wind or sun.
- May be used as a protectant against further irritation.

Warnings

- For external use only.
- To avoid contamination, do not touch tip of container to any surface. Replace cap after using.
- If solution changes color or becomes cloudy, do not use.

Stop use and ask a doctor

if you experience eye pain, changes in vision, continued redness or irritation of the eye, or if the condition worsens or persists for more than 72 hours.

Keep out of reach of children.

If swallowed, get medical help or contact a Poison Control Center right away.

Directions

Instill 1 or 2 drops in the affected eye(s) as needed.

Other information

- Use only if the imprinted seal around the bottle neck is intact and not damaged.
- Use before expiration date marked on container.
- Store at 59° - 86° F (15° - 30 C)
- RETAIN THIS PACKAGING FOR FUTURE REFERENCE.

Inactive ingredients

Boric acid; calcium chloride; magnesium chloride; potassium chloride; purified water; PURITE® (stablilized oxychloro complex); sodium borate; and sodium chloride. May also contain hydrochloric acid and/or sodium hydroxide to adjust pH.

Questions or comments?

1.800.433.8871, M-F 6 AM - 4:30 PM Pacific Time
refreshbrand.com